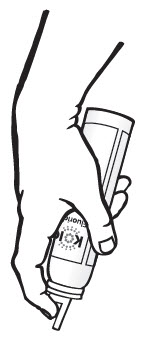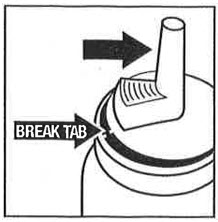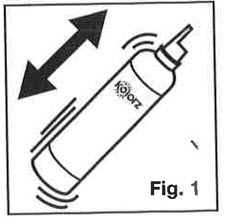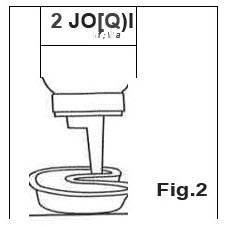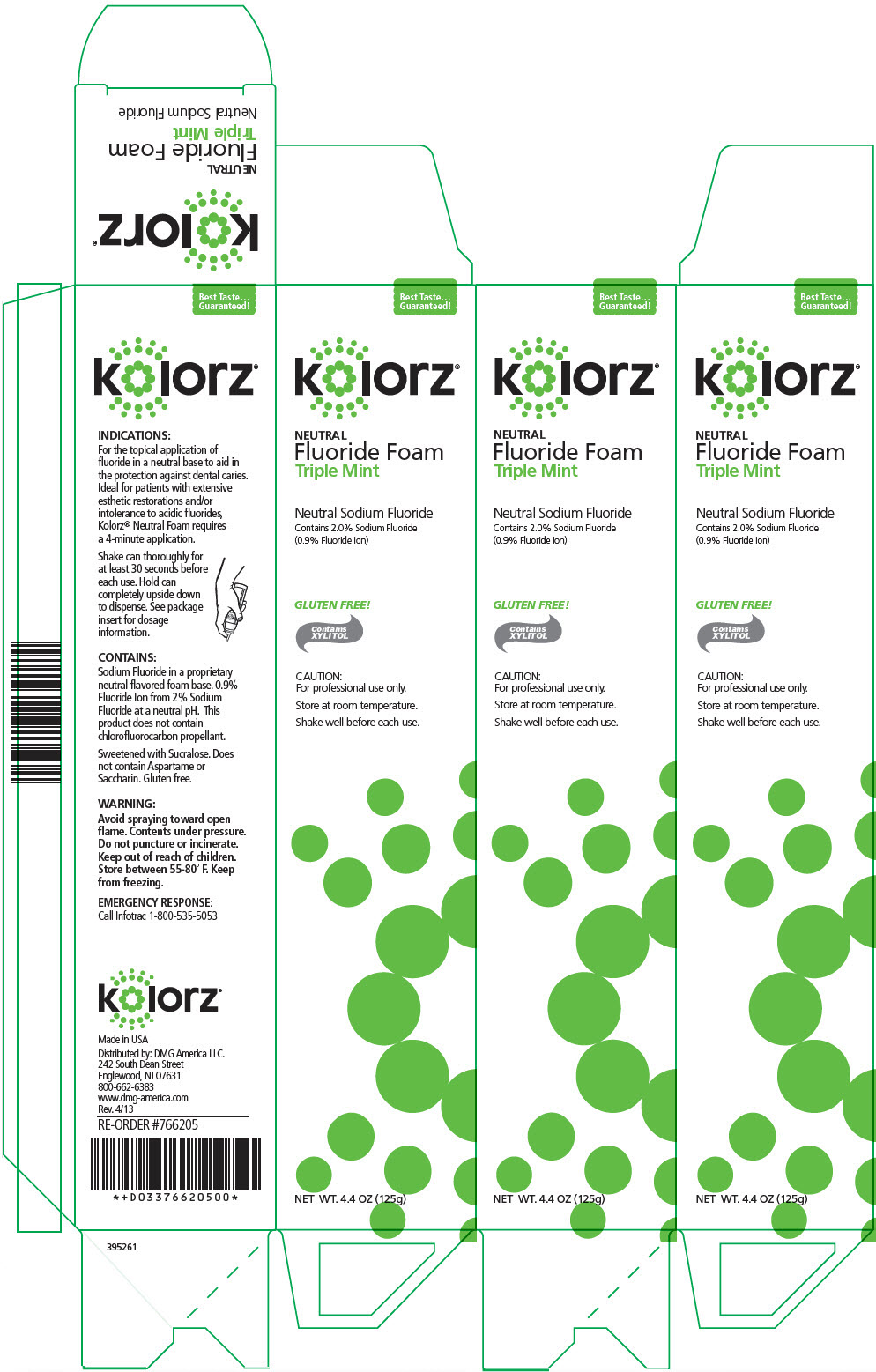 DRUG LABEL: KOLORZ NEUTRAL FLUORIDE FOAM 
NDC: 25047-765 | Form: AEROSOL, FOAM
Manufacturer: DMG AMERICA, LLC
Category: prescription | Type: HUMAN PRESCRIPTION DRUG LABEL
Date: 20211001

ACTIVE INGREDIENTS: SODIUM FLUORIDE 0.9 mg/1 g
INACTIVE INGREDIENTS: WATER; SUCRALOSE; XYLITOL

kolorz® NEUTRAL Fluoride Foam

INDICATIONS

For the topical application of fluoride in a neutral base to aid in the protection against dental caries. Ideal for patients with extensive esthetic restorations and/or intolerance to acidic fluorides, Kolorz® Neutral Foam requires a 4-minute application.

Shake can thoroughly for at least 30 seconds before each use. Hold can completely upside down to dispense. See package insert for dosage information.

CONTAINS

Sodium Fluoride in a proprietary neutral flavored foam base. 0.9% Fluoride Ion from 2% Sodium Fluoride at a neutral pH. This product does not contain chlorofluorocarbon propellant.

Sweetened with Sucralose. Does not contain Aspartame or Saccharin. Gluten free.

WARNING

Avoid spraying toward open flame. Contents under pressure. Do not puncture or incinerate. Keep out of reach of children. Store between 55-80° F. Keep from freezing.

EMERGENCY RESPONSE

Call Infotrac 1-800-535-5053

Made in USA

Distributed by: DMG America LLC.
242 South Dean Street
Englewood, NJ 07631
800-662-6383
www.dmg-america.com
Rev. 4/13

RE-ORDER #766205

INSTRUCTIONS FOR USE

kolorz®

By DMG America
Instructions For Use

Kolorz Sixty Second Fluoride Foam

Kolorz Neutral Fluoride Foam

The first time you dispense from a new bottle, gently lift upward on the nozzle to break the protective shipping tab (thin plastic tab located adjacent to "trigger"). If this tab is not broken, there could be an initial surge of foam from the dispenser.

Dosage and Administration:

1. Shake can vigorously before each use. (Fig. 1)
2. Turn can completely upside down to dispense. Point can towards fluoride applicator tray and slowly press the nozzle to fill tray. Use one press per arch, as foam will expand slightly to fill the tray. (Fig. 2)
3. Dry tooth surface and insert tray(s) in mouth.
4. For Kolorz Sixty Second Fluoride Foam: Have patient bite down lightly but firmly for 1 to 4 minutes; For Kolorz Neutral Fluoride Foam: Have patient bite down lightly but firmly for 4 minutes.
5. Remove tray(s) and have patient expectorate excess
6. Instruct patient not to eat, drink, or rinse for at least 30 minutes after application.

How Supplied: Both Kolorz Sixty Second Fluoride Foam and Kolorz Neutral Fluoride Foam are available in 4.4oz. (125g) cans and do not contain chlorofluorocarbon propellant.

Caution: For professional use only. Federal U.S.A. Law prohibits dispensing without prescription.

Warning: Contents under pressure. Do not puncture or incinerate. Store between 55-80° F. Keep from freezing.

Distributed by DMG America
242 South Dean Street
Englewood, NJ 07631 USA
Tel: 201-894-5505
Fax: 201-894-0213
www.dmg-america.com

395490 Rev. 11/13

PRINCIPAL DISPLAY PANEL - 125 g Can Carton

Best Taste...
Guaranteed!

kolorz®

NEUTRAL
Fluoride Foam
Triple Mint

Neutral Sodium Fluoride
Contains 2.0% Sodium Fluoride
(0.9% Fluoride Ion)

GLUTEN FREE!

Contains
XYLITOL

CAUTION:
For professional use only.

Store at room temperature.

Shake well before each use.

NET WT. 4.4 OZ (125g)